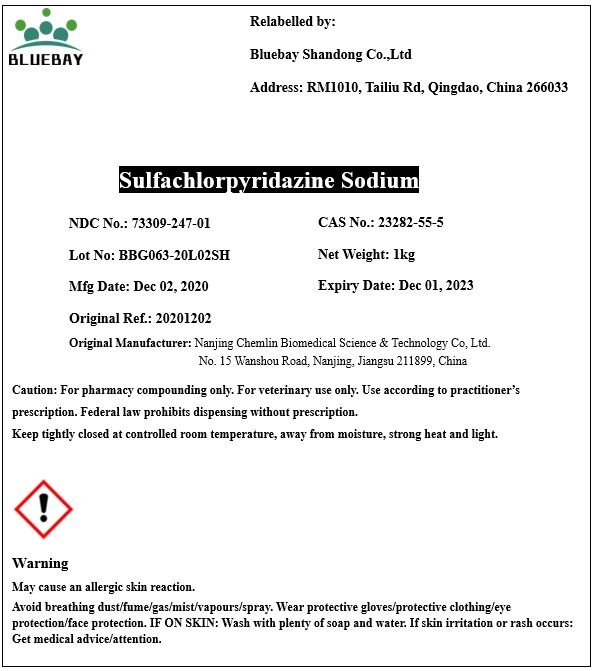 DRUG LABEL: Sulfachlorpyridazine Sodium
NDC: 73309-247 | Form: POWDER
Manufacturer: BLUEBAY SHANDONG CO.,LTD
Category: other | Type: BULK INGREDIENT
Date: 20210201

ACTIVE INGREDIENTS: SULFACHLORPYRIDAZINE SODIUM 1 kg/1 kg

Sulfachlorpyridazine Sodium